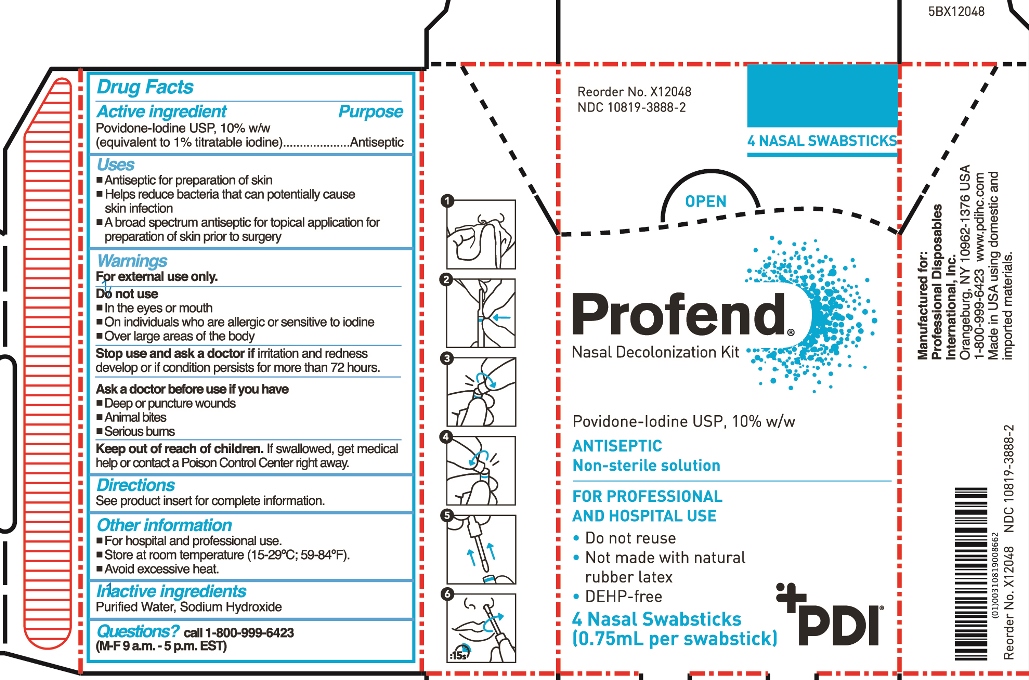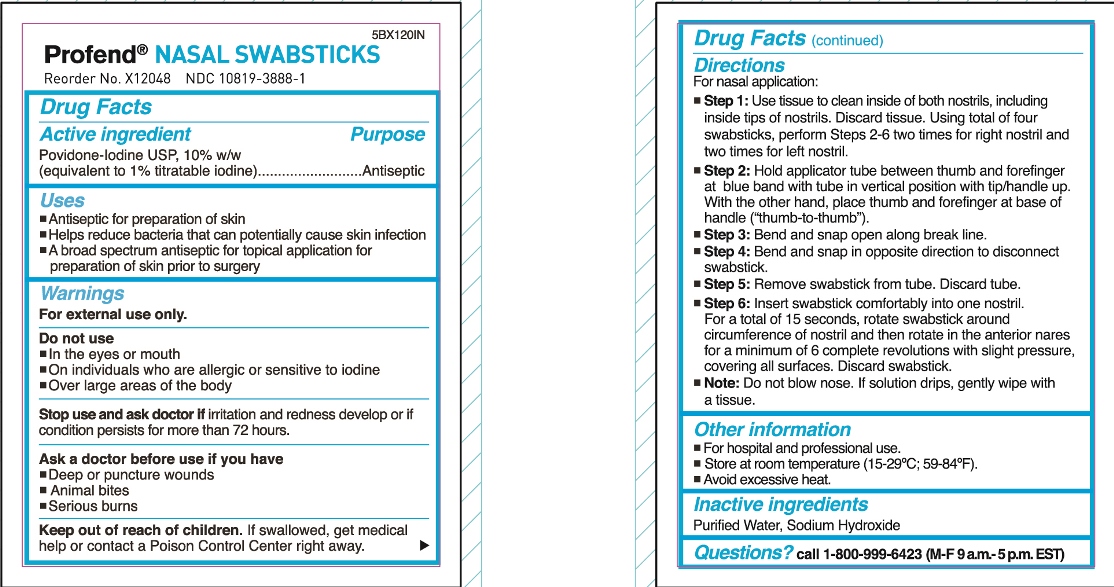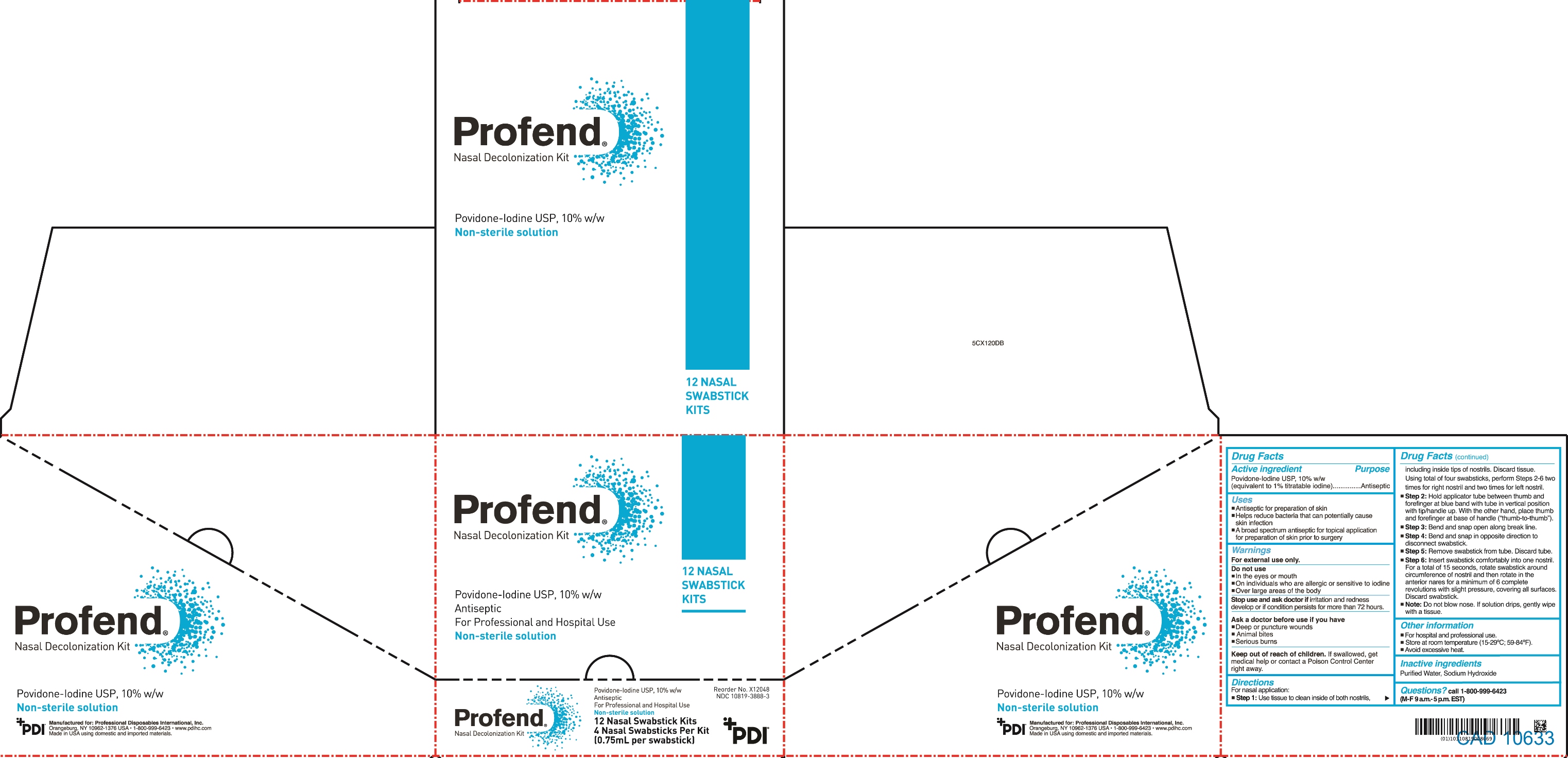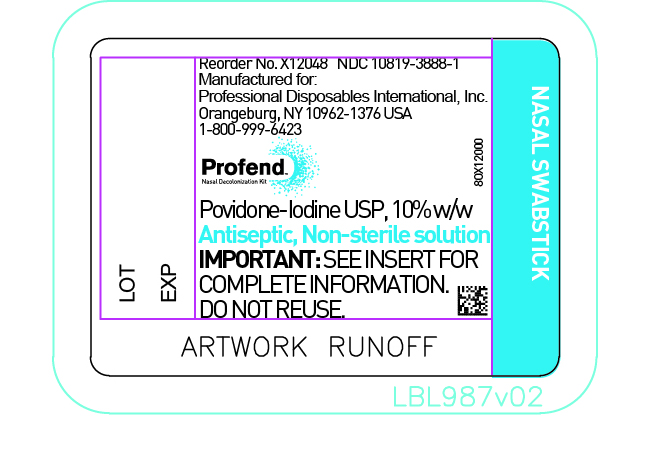 DRUG LABEL: Profend Nasal Decolonization
NDC: 10819-3888 | Form: SWAB
Manufacturer: Professional Disposables International, Inc.
Category: otc | Type: HUMAN OTC DRUG LABEL
Date: 20251002

ACTIVE INGREDIENTS: POVIDONE-IODINE 10 mg/1 mL
INACTIVE INGREDIENTS: WATER; SODIUM HYDROXIDE

Profend Nasal Decolonization Kit

Active Ingredient

Povidone-Iodine USP 10% w/w (equivalent to 1.0% titratable iodine)

Purpose

Antiseptic

Uses

- Antiseptic for preparation of skin
- Helps reduce bacteria that can potentially cause skin infection
- A broad spectrum antiseptic for topical application for preparation of skin prior to surgery

Warnings

For external use only

Do not use

- in the eyes or mouth
- on individuals who are allergic or sensitive to iodine
- over large areas of the body

Stop use and ask doctor if irritation and redness develop or if condition persists for more than 72 hours.

Ask a doctor before use if you have

- Deep or puncture wounds
- animal bites
- serious burns

Keep out of reach of children.

If swallowed, get medical help or contact a Poison Control Center right away.

Directions

For nasal application:

Step 1: Use tissue to clean inside of both nostrils, including inside tips of nostrils. Discard tissue.

Using total of four swabsticks, perform Steps 2-6 two times for right nostril and two times for left nostril.

Step 2: Hold applicator tube between thumb and forefinger at blue band with tube in vertical position with tip/handle up. With the other hand, place thumb and forefinger at base of handle (“thumb-to-thumb”).

Step 3: Bend and snap open along break line.

Step 4: Bend and snap in opposite direction to disconnect swabstick.

Step 5: Remove swabstick from tube. Discard tube.

Step 6: Insert swabstick comfortably into one nostril. For a total of 15 seconds, rotate swabstick around circumference of nostril and then rotate in the anterior nares for a minimum of 6 complete revolutions with slight pressure, covering all surfaces. Discard swabstick.

Note: Do not blow nose. If solution drips, gently wipe with a tissue.

Other information

- For hospital and professional use
- Store at room temperature (15-29oC; 59-84oF)
- Avoid excessive heat

Inactive Ingredients

Purified Water, Sodium Hydroxide

Questions?

call 1-800-999-6423 (M-F 9 a.m.-5 p.m. EST)

Principal Display Panel

Profend

Nasal Decolonization Kit

Povidone-Iodine USP, 10% w/w

Antiseptic

Non-sterile solution

Swabstick

box

carton

insert